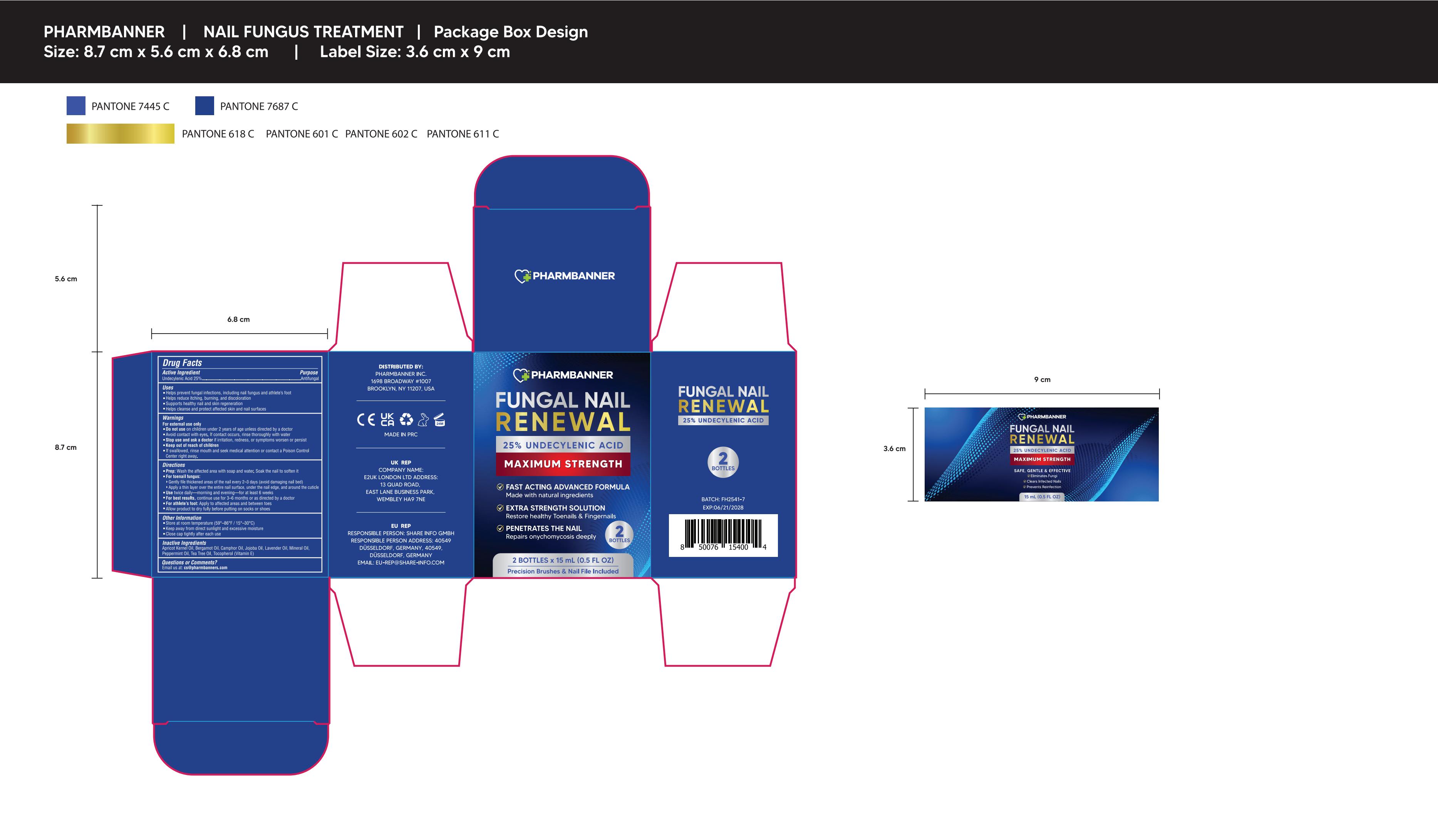 DRUG LABEL: PHARMBANNER FUNGAL NAIL RENEWAL
NDC: 83818-019 | Form: LIQUID
Manufacturer: Shenzhen Xinxin Yunhai Technology Co., Ltd.
Category: otc | Type: HUMAN OTC DRUG LABEL
Date: 20260212

ACTIVE INGREDIENTS: UNDECYLENIC ACID 25 g/100 mL
INACTIVE INGREDIENTS: ALPHA-TOCOPHEROL; PEPPERMINT OIL; CAMPHOR OIL; APRICOT KERNEL OIL; TEA TREE OIL; LAVENDER OIL; MINERAL OIL; JOJOBA OIL; BERGAMOT OIL

83818-019 Update Manufacturer

Active Ingredient

Undecylenic Acid 25%

Purpose

Antifungal

Use

■ Helps prevent fungal infections, including nail fungus and athlete's foot
■ Helps reduce itching, burning, and discoloration
■ Supports healthy nail and skin regeneration
■ Helps cleanse and protect affected skin and nail surfaces

Warnings

For external use only

Do not use

on children under 2 years of age unless directed by a doctor

When Using

Avoid contact with eyes. If contact occurs, rinse thoroughly with water

Stop Use

if irritation, redness, or symptoms worsen or persist

Ask Doctor

if irritation, redness, or symptoms worsen or persist

Keep Out Of Reach Of Children

If swallowed, rinse mouth and seek medical attention or contact a Poison Control Center right away.

Directions

■ Prep: Wash the affected area with soap and water. Soak the nail to soften it
■ For toenail fungus:
▸ Gently file thickened areas of the nail every 2-3 days (avoid damaging nail bed)
▸ Apply a thin layer over the entire nail surface, under the nail edge, and around the cuticle
■ Use twice daily-morning and evening for at least 6 weeks
■ For best results, continue use for 3-6 months or as directed by a doctor
■ For athlete's foot: Apply to affected areas and between toes
■ Allow product to dry fully before putting on socks or shoes

Other information

■ Store at room temperature (59°-86°F / 15°-30°C)
■ Keep away from direct sunlight and excessive moisture
■Close cap tightly after each use

Inactive ingredients

Apricot Kernel Oil, Bergamot Oil, Camphor Oil, Jojoba Oil, Lavender Oil, Mineral Oil, Peppermint Oil, Tea Tree Oil, Tocopherol (Vitamin E)

Questions

Email us: cs@pharmbanners.com